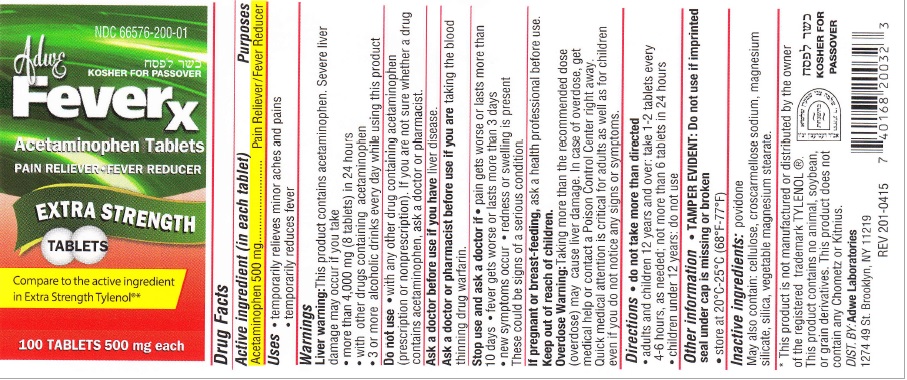 DRUG LABEL: Adwe Feverx
NDC: 66576-200 | Form: TABLET
Manufacturer: Syntho Pharmaceuticals, Inc.
Category: otc | Type: HUMAN OTC DRUG LABEL
Date: 20200204

ACTIVE INGREDIENTS: ACETAMINOPHEN 500 mg/1 1
INACTIVE INGREDIENTS: POVIDONE; POWDERED CELLULOSE; CROSCARMELLOSE SODIUM; MAGNESIUM SILICATE; SILICON DIOXIDE; MAGNESIUM STEARATE

ACETAMINOPHEN 500 MG TABLET

Drug Facts

Active ingredient (in each tablet)

Acetaminophen 500 mg

Purpose

Pain Reliever/Fever Reducer

Uses

- temporarily relieves minor aches and pains
- temporarily reduces fever

Warnings

Liver warning: This product contains acetaminophen. Severe liver damage may occur if you take

- more than 4,000 mg (8 tablets) in 24 hours
- with other drugs containing acetaminophen
- 3 or more alcoholic drinks every day while using this product

Do not use

with any other drug containing acetaminophen (prescription or nonprescription). If you are not sure whether a drug contains acetaminophen, ask a doctor or pharmacist.

Ask a doctor before use if you have

liver disease

Ask a doctor or pharmacist before use if you are

taking blood thinning drug warfarin

Stop use and ask a doctor if

- pain gets worse or lasts more than 10 days

- fever gets worse or lasts more than 3 days

- new symptoms occur

- redness or swelling is present

These could be signs of a serious condition.

If pregnant or breast-feeding

ask a health professional before use.

Keep out of reach of children

Overdose Warning

Taking more than therecommended dose (overdose) may cause liver damage. In case of overdose get medical help or contact Poison Control Centre right away. Quick medical attention is critical for adults as well as for children even if you do not notice any signs or symptoms.

Directions

do not take more than directed (see overdose warning)

adults & children 12 years and over:

- take 1-2 tablets every 4-6 hours as needed
- do not take more than 6 tablets in 24 hours

children under 12 years: do not use

Other information

TAMPER EVIDENT: Do not use if imprinted seal under cap is missing or broken.

- store at 20ºC - 25ºC (68ºF - 77ºF)

Inactive ingredients

povidone. May also contain: cellulose, croscarmellose sodium, magnesium silicate, silica, vegetable magnesium starate

* This product is not manufactured or distributed by the owner of the registered trademark TYLENOL®. This products contain no animal, soybean or grain derivatives. THis product does not contains any Chometz or Kitnius.

KOSHER FOR PASSOVER

DIST BY: Adwe Laboratories

1274 49 St. Brooklyn, NY 11219

REV 201-0415

PRINCIPAL DISPLAY PANEL

NDC 666576-200-01

KOSHER FOR PASSOVER

Adwe Feverx

Acetaminophen Tablets

PAIN RELIEVER FEVER REDUCER

EXTRA STRENGTH TABLETS

Compare to Active Ingredient in Extra Strength Tylenol®*

100 TABLETS 500 mg each